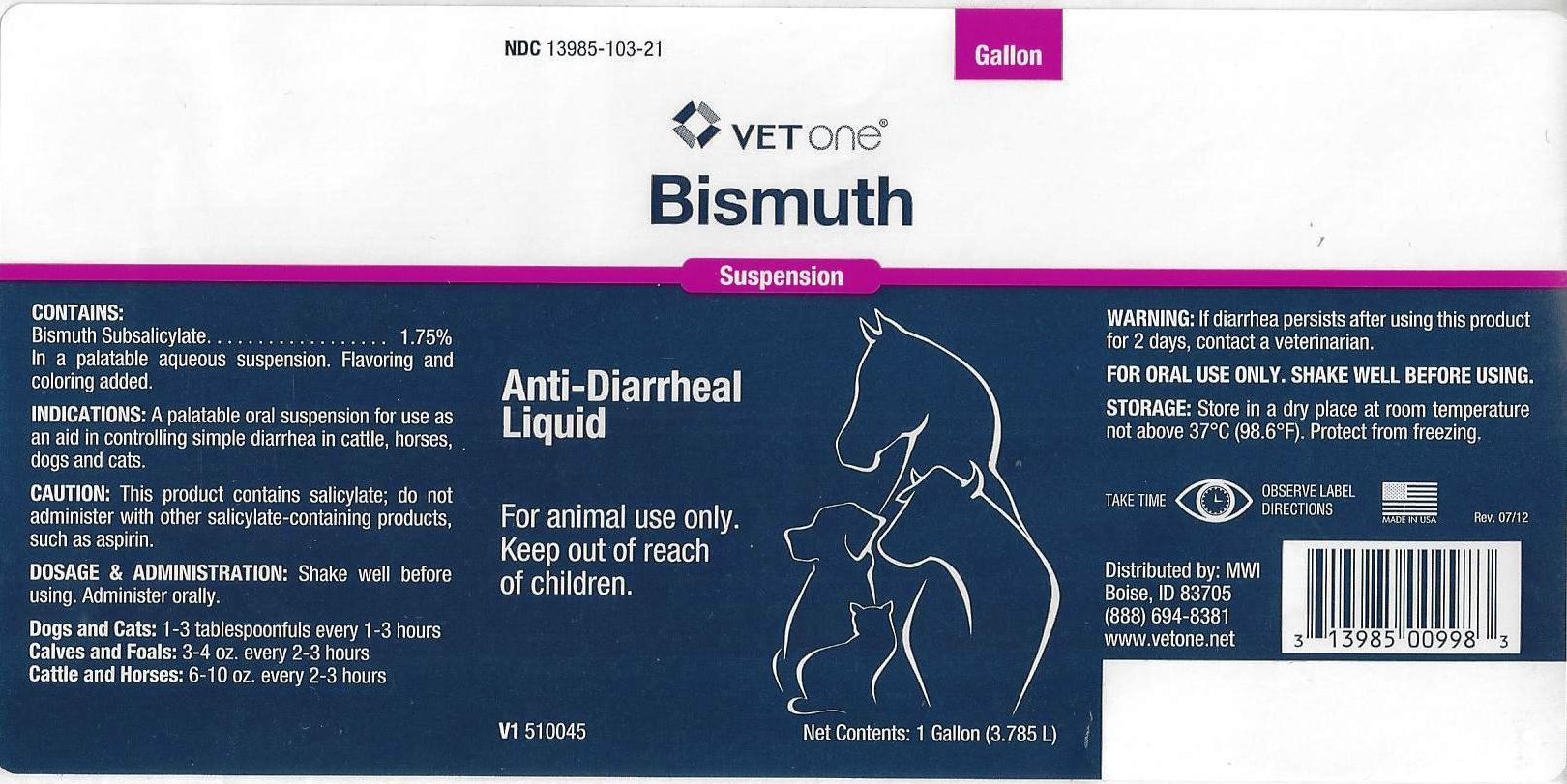 DRUG LABEL: Bismuth
NDC: 13985-103 | Form: SUSPENSION
Manufacturer: MWI/VetOne
Category: animal | Type: OTC ANIMAL DRUG LABEL
Date: 20130917

ACTIVE INGREDIENTS: BISMUTH SUBSALICYLATE 18 mg/1 mL
INACTIVE INGREDIENTS: GUAR GUM; POTASSIUM SORBATE; SACCHARIN SODIUM; METHYL SALICYLATE; WATER; D&C RED NO. 33; SILICON DIOXIDE

VETone® Bismuth

NDC 13985-103-21 VET one Bismuth Suspension Anti-Diarrheal Liquid

For animal use only.

Keep out of reach of children.

V1 510045

Net Contents: 1 Gallon (3.785L)

CONTAINS:

Bismuth Subsalicylate ... 1.75%

In a palatable aqueous suspension. Flavoring and coloring added.

INDICATIONS:

A palatable oral suspension for use as an aid in controlling simple diarrhea in cattle, horses, dogs and cats

CAUTION:

This product contains salicylate; do not administer with other salicylate-containing products, such as aspirin.

DOSAGE & ADMINISTRATION:

Shake well before using. Administer orally.

Dogs and Cats: 1 to 3 tablespoonfuls every 1-3 hours

Calves and Foals: 3 to 4 oz. every 2-3 hours

Cattle and Horses: 6 to 10 oz. every 2-3 hours

WARNING:

If diarrhea persists after using this product for 2 days, contact a veterinarian.

FOR ORAL USE ONLY. SHAKE WELL BEFORE USING.

STORAGE:

Store in a dry place at room temperature not above 37ºC (98.6ºF). Protect from freezing.

TAKE TIME OBSERVE LABEL DIRECTIONS

MADE IN USA Rev. 07/12

Distributed by: MWI

Boise, ID 83705
(888) 694-8381
www.vetone.net

Bottle Label

Bottle Label